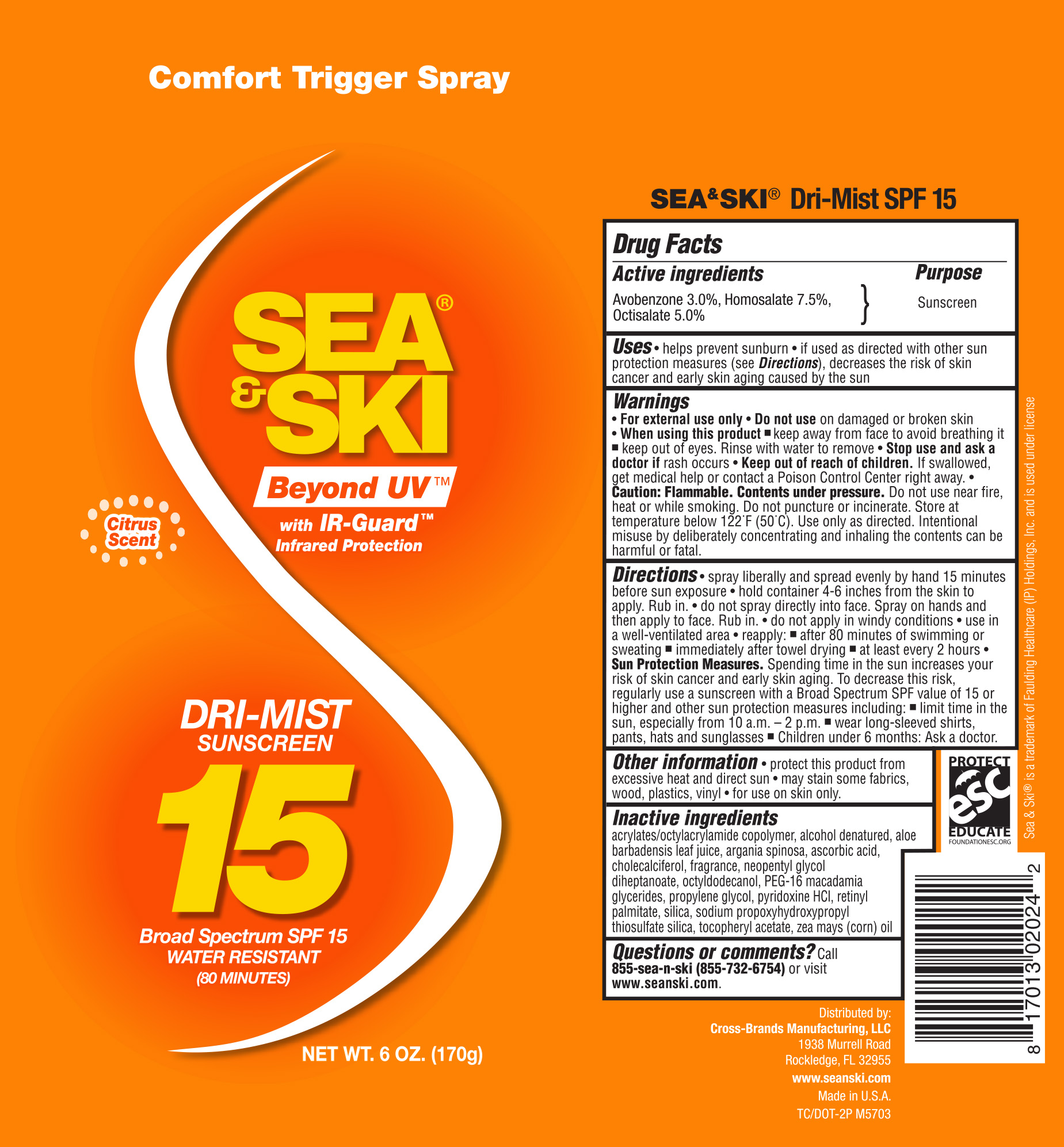 DRUG LABEL: SPF 15
NDC: 71153-2014 | Form: AEROSOL, SPRAY
Manufacturer: Cross-Brands Manufacturing, LLC
Category: otc | Type: HUMAN OTC DRUG LABEL
Date: 20190108

ACTIVE INGREDIENTS: HOMOSALATE 7.5 g/1 mL; AVOBENZONE 3 g/1 mL; OCTISALATE 5 g/1 mL
INACTIVE INGREDIENTS: ALOE VERA LEAF 0.1 g/1 mL

Sea & Ski SPF 15 Spray